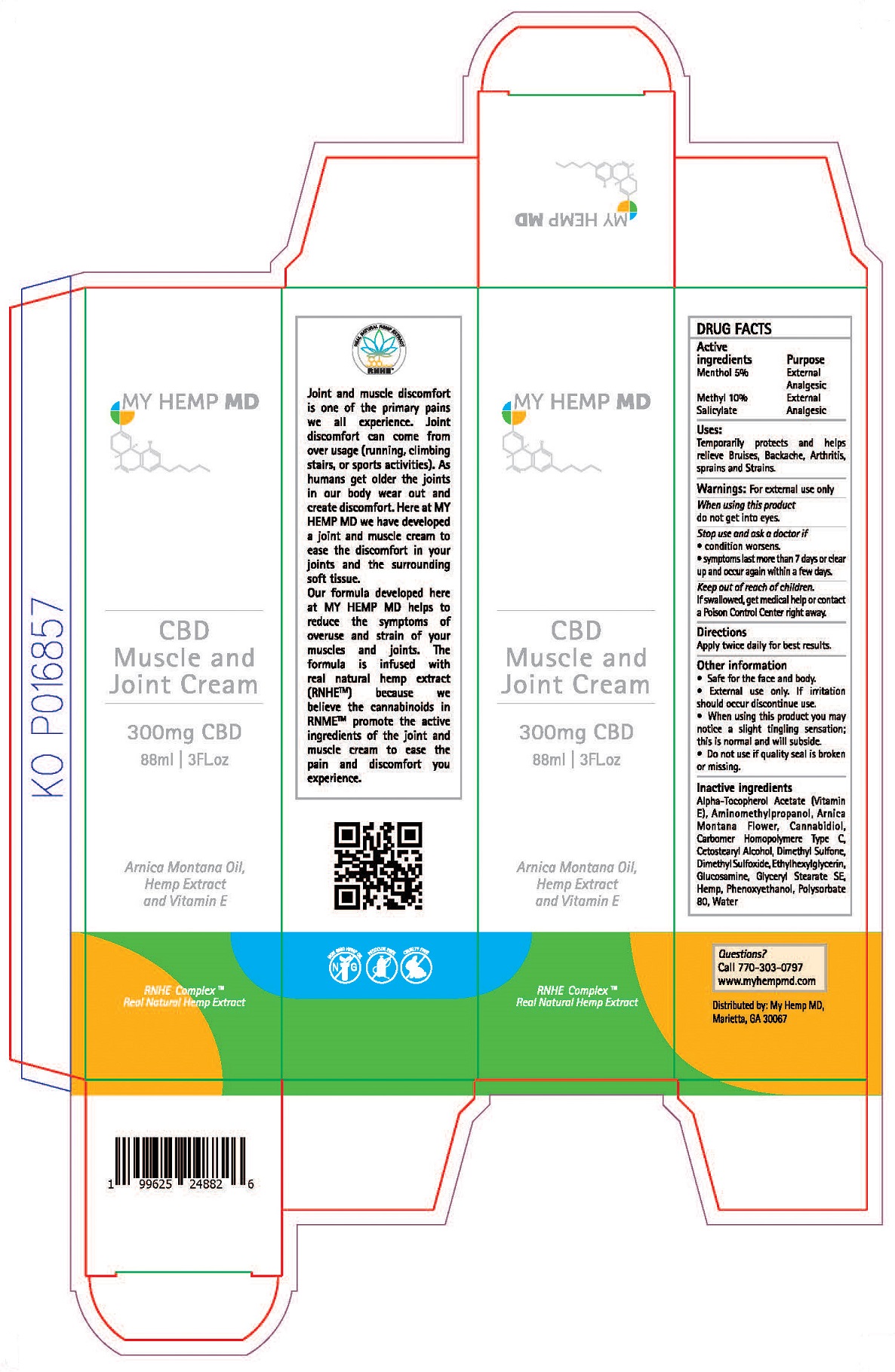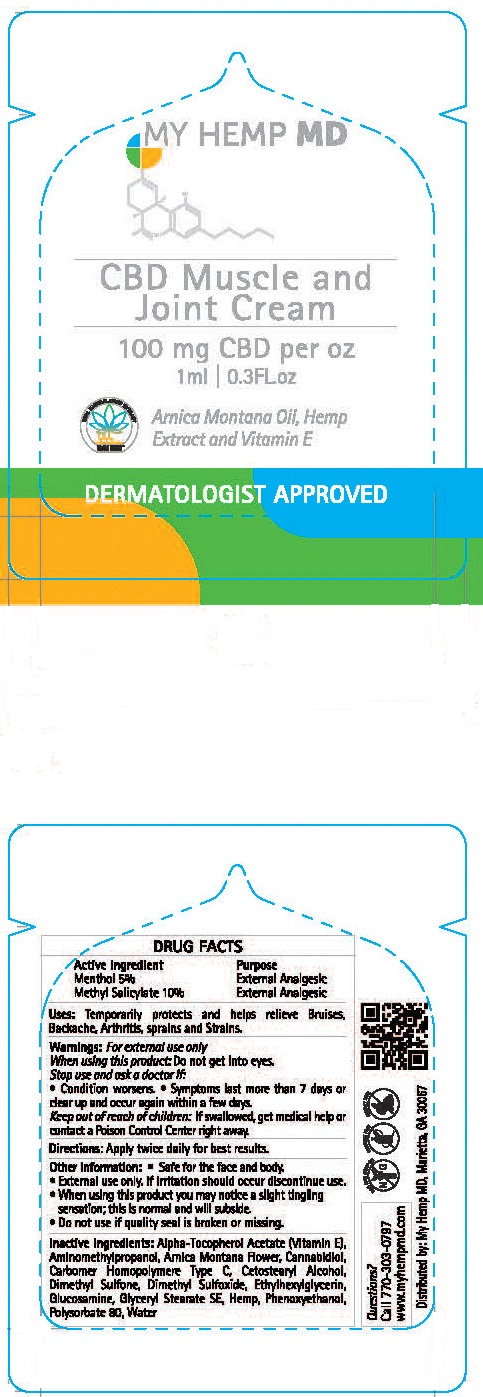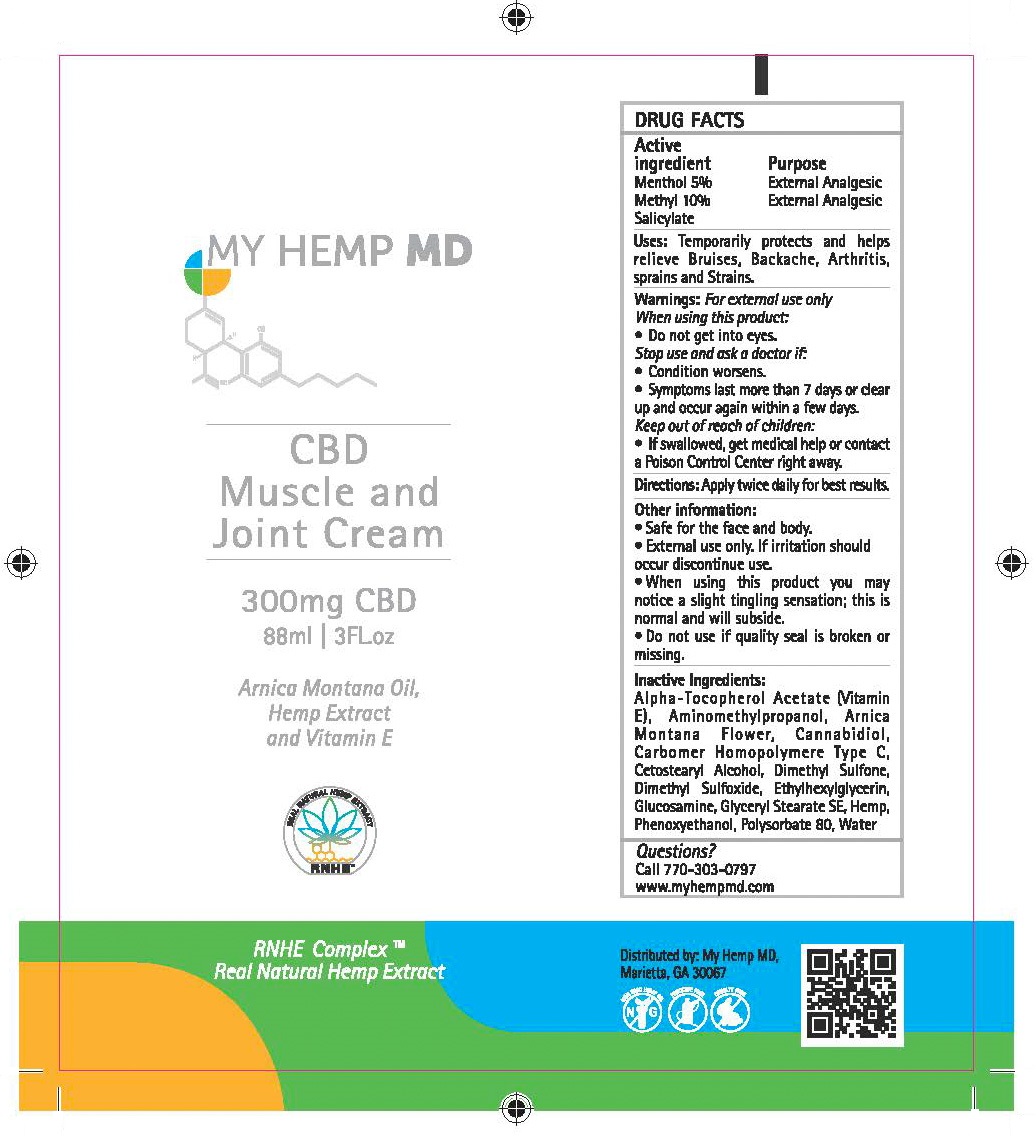 DRUG LABEL: My Hemp MD CBD Muscle and Joint Cream
NDC: 52261-5201 | Form: CREAM
Manufacturer: Cosco International, Inc.
Category: otc | Type: HUMAN OTC DRUG LABEL
Date: 20191101

ACTIVE INGREDIENTS: MENTHOL 0.05 1/1 kg; METHYL SALICYLATE 0.10 kg/1 kg
INACTIVE INGREDIENTS: WATER; CARBOMER COPOLYMER TYPE C (ALLYL PENTAERYTHRITOL CROSSLINKED); DIMETHYL SULFONE; DIMETHYL SULFOXIDE; N-ACETYLGLUCOSAMINE; GLYCERYL MONOSTEARATE; POLYSORBATE 80; CETOSTEARYL ALCOHOL; ARNICA MONTANA FLOWER; HEMP; CANNABIDIOL; .ALPHA.-TOCOPHEROL ACETATE, DL-; PHENOXYETHANOL; ETHYLHEXYLGLYCERIN; AMINOMETHYLPROPANOL

Drug Facts

ACTIVE INGREDIENT

Acrive Ingredients....................Purpose

Menthol 5%................................External Analgesic

Methyl Salicylate 10%..................External Analgesic

PURPOSE

External Analgesic

INDICATIONS AND USAGE

Uses: Temporarily helps relieve minor aches and pains of muscle and joints associated with simple backaches, arthritis, sprains, bruises and strains.

Warnings:

For external use only

When using tthis product:

- Do not get into eyes.

Stop use and ask a doctor if:

- Condition worsens
- Symptoms last more than 7 days or clear up and occur again within a few days.

Keep out of reach of children:

- If swallowed, get medical help or contact a Poison Control Center right away.

Directions:

Apply twice daily for best results.

Other information:

- External use only. If irratation should occur discontinue use.
- When using this product you may notice a slight tingling sensation; this is normal and will subside.
- Do not use if quality seal is broken or missing.

Inactive ingredients:

Alpha-Tocopherol Acetate (Vitamin E), Aminomethylpropanol, Arnica Montana Flower, Cannabidiol, Carbomer Homopolymere Type C, Cetostearyl Alcohol, Dimethyl Sulfone, Dimethyl Sulfoxide, Ethylhexylglycerin, Glucosamine, Glyceryl Monostearate, Hemp, Phenoxyethanol, Polysorbate 80, Water

Questions?

Call 770-303-0797

www.myhempmd.com

Distributed by: My Hemp MD

Marietta, GA 30067